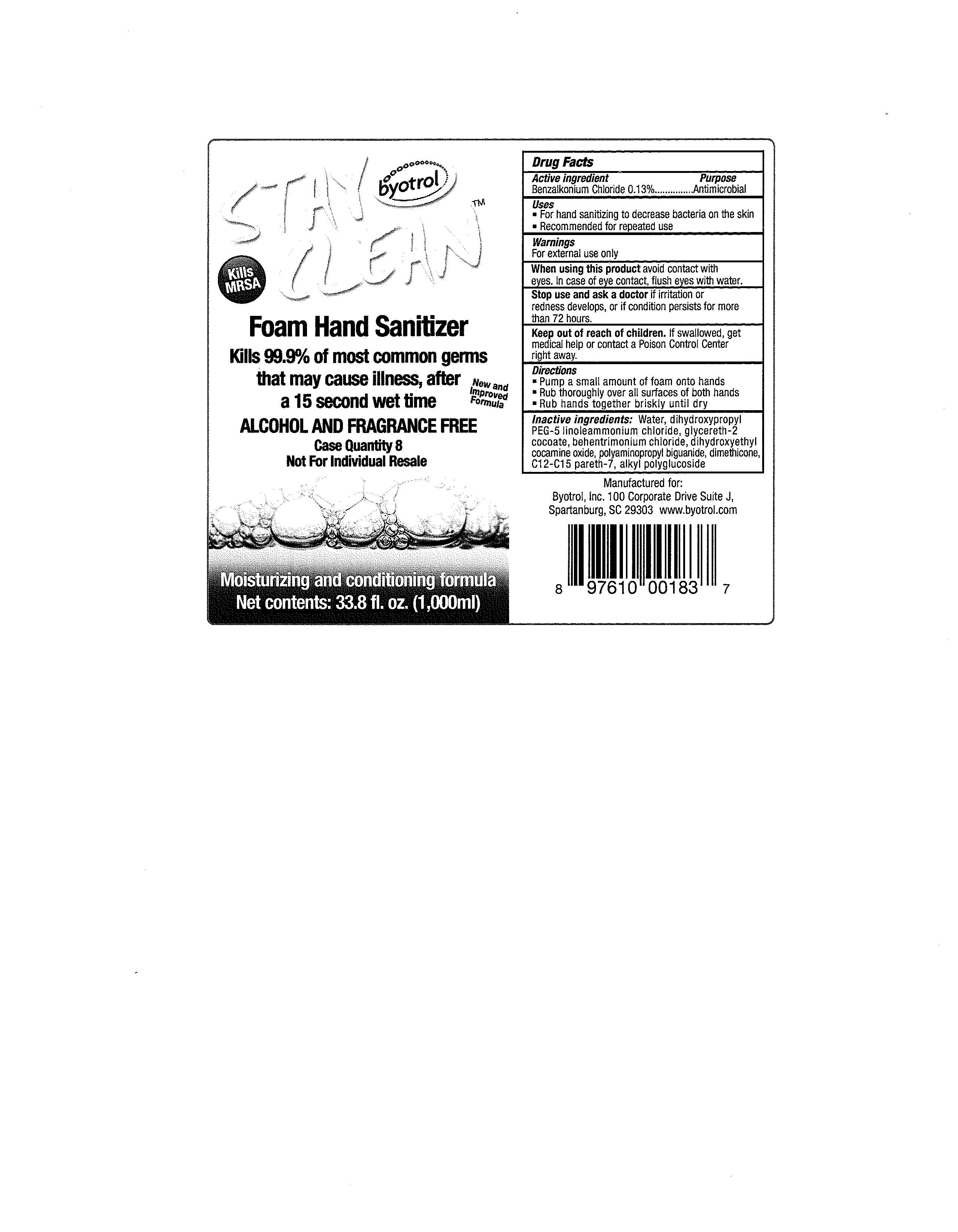 DRUG LABEL: Stay Clean Foam Hand Sanitizer
NDC: 42719-345 | Form: LIQUID
Manufacturer: Byotrol, Inc.
Category: otc | Type: HUMAN OTC DRUG LABEL
Date: 20091031

ACTIVE INGREDIENTS: Benzalkonium Chloride 0.13 mL/100 mL
INACTIVE INGREDIENTS: Dimethicone; Water

Drug Facts

Active ingredient Purpose

Benzalkonium Chloride 0.13%....................Antimicrobial

Uses

For hand sanitizing to decrease bacteria on the skin

Recommended for repeated use

Warnings
For external use only

When using this product avoid contact with eyes. In case of eye contact, flush eyes with water.

Stop use and ask a doctor if irritation or redness develops, or if conditions persists for more than 72 hours.

Keep out of reach of children. If swallowed, get medical help or contact a Poison Control Center right away.

Directions

Pump a small amount of foam onto hands

Rub thoroughly over all surfaces of both hands

Rub hands together briskly until dry

Inactive ingredients:

Water, dihydroxypropyl PEG-5 linoleammonium chloride, glycereth-2 cocoate, behentrimonium chloride, dihydroxyethyl cocamine oxide, polyaminopropyl biguanide, dimethicone, C12-C15 pareth-7, alkyl polyglucoside

PACKAGE LABEL

Stay Clean Foam Sanitizer

byotrol

Kills MRSA

Kills 99.9% of common germs that may cause illness, after a 15 second wet time

New and Improved Formula

Alcohol and Fragrance Free

Case Quantity 8

Not For Individual Resale

Moisturizing and conditioning formula

Net contents: 33.8 fl. oz. (1,000ml)